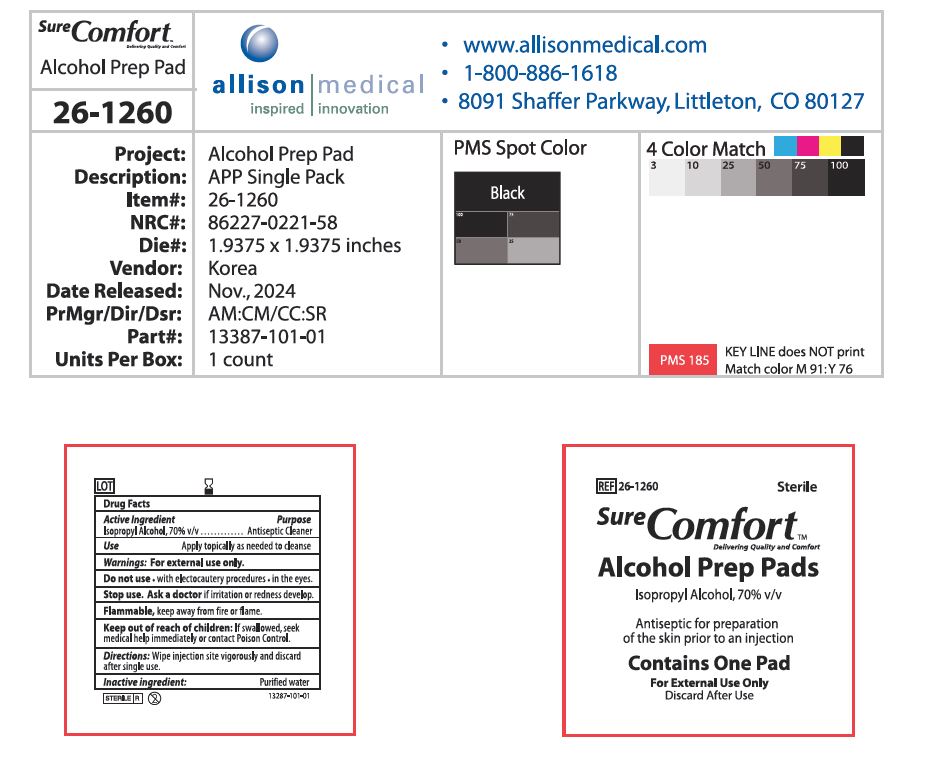 DRUG LABEL: Sure Comfort Alcohol Prep Pads
NDC: 77039-032 | Form: LIQUID
Manufacturer: IDO PHARM
Category: otc | Type: HUMAN OTC DRUG LABEL
Date: 20260105

ACTIVE INGREDIENTS: ISOPROPYL ALCOHOL 70 mL/100 mL
INACTIVE INGREDIENTS: WATER

ACTIVE INGREDIENT

isopropyl alcohol 70%

INACTIVE INGREDIENT

Water

PURPOSE

apply topically as needed to cleanse

Keep out of reach of children

INDICATIONS AND USAGE

wipe injection site vigorously and discard after single use

WARNINGS

Flammable, keep away from fire and flames
For external use only

DOSAGE AND ADMINISTRATION

For external use only